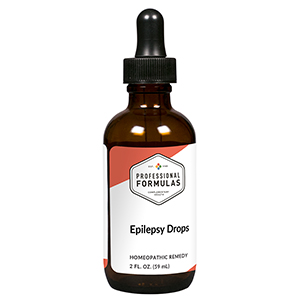 DRUG LABEL: Epilepsy Drops
NDC: 63083-2020 | Form: LIQUID
Manufacturer: Professional Complementary Health Formulas
Category: homeopathic | Type: HUMAN OTC DRUG LABEL
Date: 20190815

ACTIVE INGREDIENTS: ASTERIAS RUBENS 4 [hp_X]/59 mL; AMARYLLIS BELLADONNA WHOLE 4 [hp_X]/59 mL; HYOSCYAMUS NIGER 4 [hp_X]/59 mL; OYSTER SHELL CALCIUM CARBONATE, CRUDE 6 [hp_X]/59 mL; CAUSTICUM 6 [hp_X]/59 mL; CICUTA VIROSA WHOLE 6 [hp_X]/59 mL; OENANTHE CROCATA WHOLE 6 [hp_X]/59 mL; ARTEMISIA VULGARIS ROOT 12 [hp_X]/59 mL; COPPER 12 [hp_X]/59 mL; LEAD 12 [hp_X]/59 mL; ZINC 12 [hp_X]/59 mL
INACTIVE INGREDIENTS: ALCOHOL; WATER

C20

ACTIVE INGREDIENTS

Asterias rubens 4X
Belladonna 4X
Hyoscyamus niger 4X
Calcarea carbonica 6X
Causticum 6X
Cicuta virosa 6X
Oenanthe crocata 6X
Artemisia vulgaris 12X
Cuprum metallicum 12X
Plumbum metallicum 12X
Zincum metallicum 12X

QUESTIONS

Professional Formulas

PO Box 2034 Lake Oswego, OR 97035

INDICATIONS

For the temporary relief of muscle twitches, spasms, cramps, fatigue, or headache.*

PURPOSE

*Claims based on traditional homeopathic practice, not accepted medical evidence. Not FDA evaluated.

WARNINGS

Persistent symptoms may be a sign of a serious condition. If symptoms persist or worsen, consult a doctor. Keep out of the reach of children. In case of overdose, get medical help or contact a poison control center right away. If pregnant or breastfeeding, ask a healthcare professional before use.

Keep out of the reach of children.

PREGNANCY OR BREAST FEEDING

If pregnant or breastfeeding, ask a healthcare professional before use.

DIRECTIONS

Place drops under tongue 30 minutes before/after meals. Adults and children 12 years and over: Take 10 drops up to 3 times per day for up to 6 weeks. For immediate onset of symptoms, take 10 to 15 drops every 15 minutes up to 3 hours. For less severe symptoms, take 10-15 drops hourly up to 8 hours. Consult a physician for use in children under 12 years of age.

OTHER INFORMATION

Tamper resistant. If seal is broken, do not use. After opening, close container tightly and store at room temperature away from heat.

INACTIVE INGREDIENTS

20% ethanol, purified water.

LABEL

Est 1985

Professional Formulas

Complementary Health

Epilepsy Drops

Homeopathic Remedy

2 FL. OZ. (59 mL)